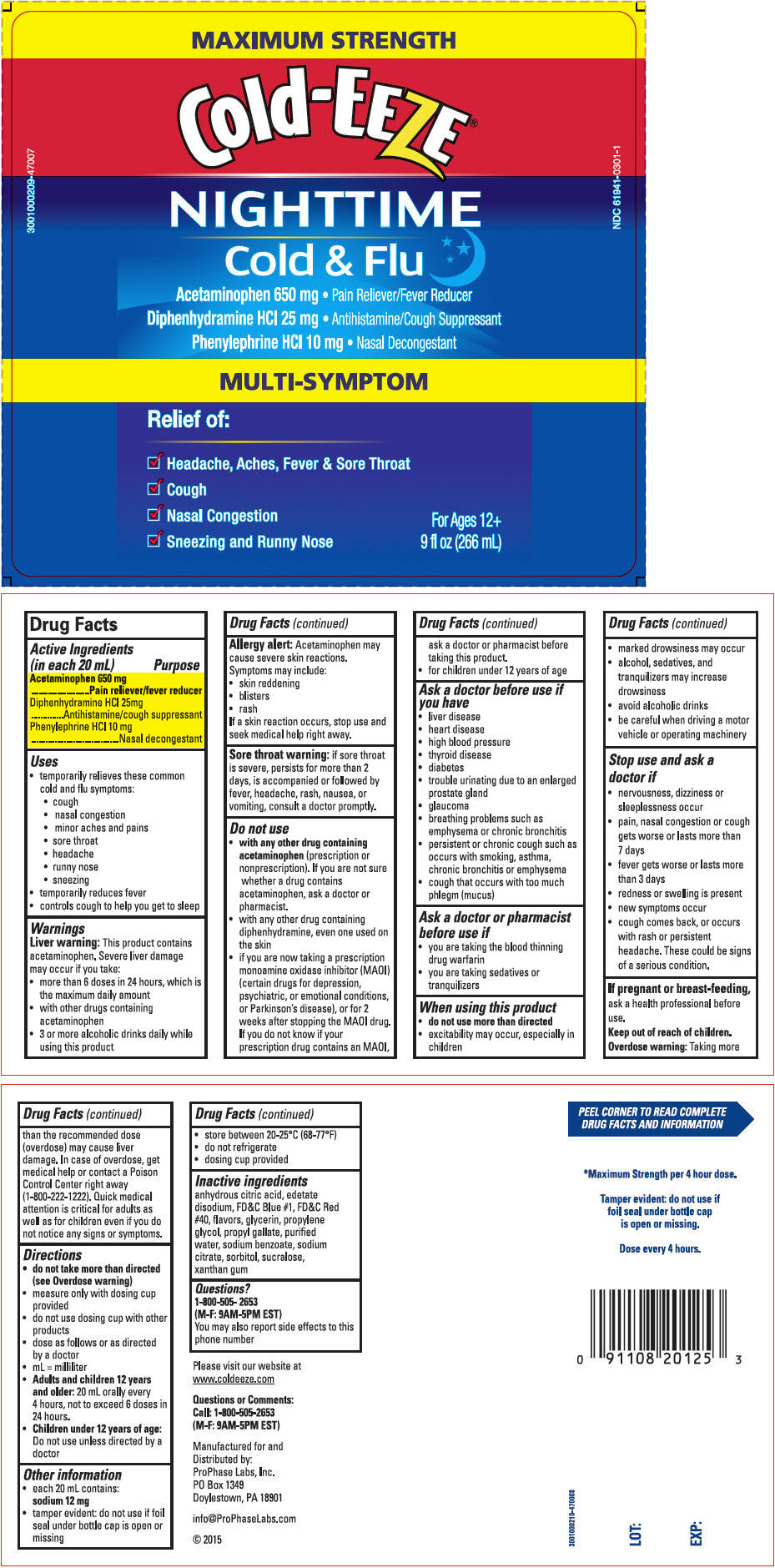 DRUG LABEL: Cold-EEZE 
NDC: 61941-0301 | Form: LIQUID
Manufacturer: ProPhase Labs, Inc.
Category: otc | Type: HUMAN OTC DRUG LABEL
Date: 20160129

ACTIVE INGREDIENTS: Acetaminophen 650 mg/20 mL; Diphenhydramine Hydrochloride 25 mg/20 mL; Phenylephrine Hydrochloride 10 mg/20 mL
INACTIVE INGREDIENTS: Anhydrous Citric Acid; Edetate Disodium; FD&C Blue NO. 1; FD&C Red NO. 40; Glycerin; Propylene Glycol; Propyl Gallate; Water; Sodium Benzoate; Sodium Citrate, Unspecified Form; Sorbitol; Sucralose; Xanthan Gum

Cold-EEZE®
Nighttime Cold & Flu

Drug Facts

ACTIVE INGREDIENT

Active Ingredients (in each 20 mL) | Purpose
Acetaminophen 650 mg | Pain reliever/fever reducer
Diphenhydramine HCl 25mg | Antihistamine/cough suppressant
Phenylephrine HCl 10 mg | Nasal decongestant

Uses

- temporarily relieves these common cold and flu symptoms:
  - cough
  - nasal congestion
  - minor aches and pains
  - sore throat
  - headache
  - runny nose
  - sneezing
- temporarily reduces fever
- controls cough to help you get to sleep

Warnings

Liver warning

This product contains acetaminophen. Severe liver damage may occur if you take:

- more than 6 doses in 24 hours, which is the maximum daily amount
- with other drugs containing acetaminophen
- 3 or more alcoholic drinks daily while using this product

Allergy alert

Acetaminophen may cause severe skin reactions.

Symptoms may include:

- skin reddening
- blisters
- rash

If a skin reaction occurs, stop use and seek medical help right away.

Sore throat warning: if sore throat is severe, persists for more than 2 days, is accompanied or followed by fever, headache, rash, nausea, or vomiting, consult a doctor promptly.

Do not use

- with any other drug containing acetaminophen (prescription or nonprescription). If you are not sure whether a drug contains acetaminophen, ask a doctor or pharmacist.
- with any other drug containing diphenhydramine, even one used on the skin
- if you are not taking a prescription monoamine oxidase inhibitor (MAOI) (certain drugs for depression, psychiatric, or emotional conditions, or Parkinson's disease), or for 2 weeks after stopping the MAOI drug. If you do not know if your prescription drug contains an MAOI, ask a doctor or pharmacist before taking this product.
- for children under 12 years of age

Ask a doctor before use if you have

- liver disease
- heart disease
- high blood pressure
- thyroid disease
- diabetes
- trouble urinating due to an enlarged prostate gland
- glaucoma
- breathing problems such as emphysema or chronic bronchitis
- persistent or chronic cough such as occurs with smoking, asthma, chronic bronchitis or emphysema
- cough that occurs with too much phlegm (mucus)

Ask a doctor or pharmacist before use if

- you are taking the blood thinning drug warfarin
- you are taking sedatives or tranquilizers

When using this product

- do not use more than directed
- excitability may occur, especially in children
- marked drowsiness may occur
- alcohol, sedatives, and tranquilizers may increase drowsiness
- avoid alcoholic drinks
- be careful when driving a motor vehicle or operating machinery

Stop use and ask a doctor if

- nervousness, dizziness or sleeplessness occur
- pain, nasal congestion or cough gets worse or lasts more than 7 days
- fever gets worse or lasts more than 3 days
- redness or swelling is present
- new symptoms occur
- cough comes back, or occurs with rash or persistent headache. These could be signs of a serious condition.

PREGNANCY OR BREAST FEEDING

If pregnant or breast-feeding, ask a health professional before use.

Keep out of reach of children.

Overdose warning

Taking more than the recommended dose (overdose) may cause liver damage. In case of overdose, get medical help or contact a Poison Control Center right away (1-800-222-1222). Quick medical attention is critical for adults as well as for children even if you do not notice any signs or symptoms.

Directions

- do not take more than directed (see Overdose warning)
- measure only with dosing cup provided
- do not use dosing cup with other products
- dose as follows or as directed by a doctor
- mL = milliliter
- Adults and children 12 years and older: 20 mL orally every 4 hours, not to exceed 6 doses in 24 hours.
- Children under 12 years of age: Do not use unless directed by a doctor

Other information

- each 20 mL contains: sodium 12 mg
- tamper evident: do not use if foil seal under bottle cap is open or missing
- store between 20-25°C (68-77°F)
- do not refrigerate
- dosing cup provided

Inactive ingredients

anhydrous citric acid, edetate disodium, FD&C Blue #1, FD&C Red #40, flavors, glycerin, propylene glycol, propyl gallate, purified water, sodium benzoate, sodium citrate, sorbitol, sucralose, xanthan gum

Questions?

1-800-505- 2653
(M-F: 9AM-5PM EST)

You may also report side effects to this phone number

Distributed by:
ProPhase Labs, Inc.
PO Box 1349
Doylestown, PA 18901

PRINCIPAL DISPLAY PANEL - 266 mL Bottle Label

MAXIMUM STRENGTH

Cold-EEZE®

NIGHTTIME
Cold & Flu

Acetaminophen 650 mg • Pain Reliever/Fever Reducer

Diphenhydramine HCl 25 mg • Antihistamine/Cough Suppressant

Phenylephrine HCl 10 mg • Nasal Decongestant

MULTI-SYMPTOM

Relief of:

✓ Headache, Aches, Fever & Sore Throat
✓ Cough
✓ Nasal Congestion
✓ Sneezing and Runny Nose

For Ages 12+
9 fl oz (266 mL)

3001000209-47007

NDC 61941-0301-1